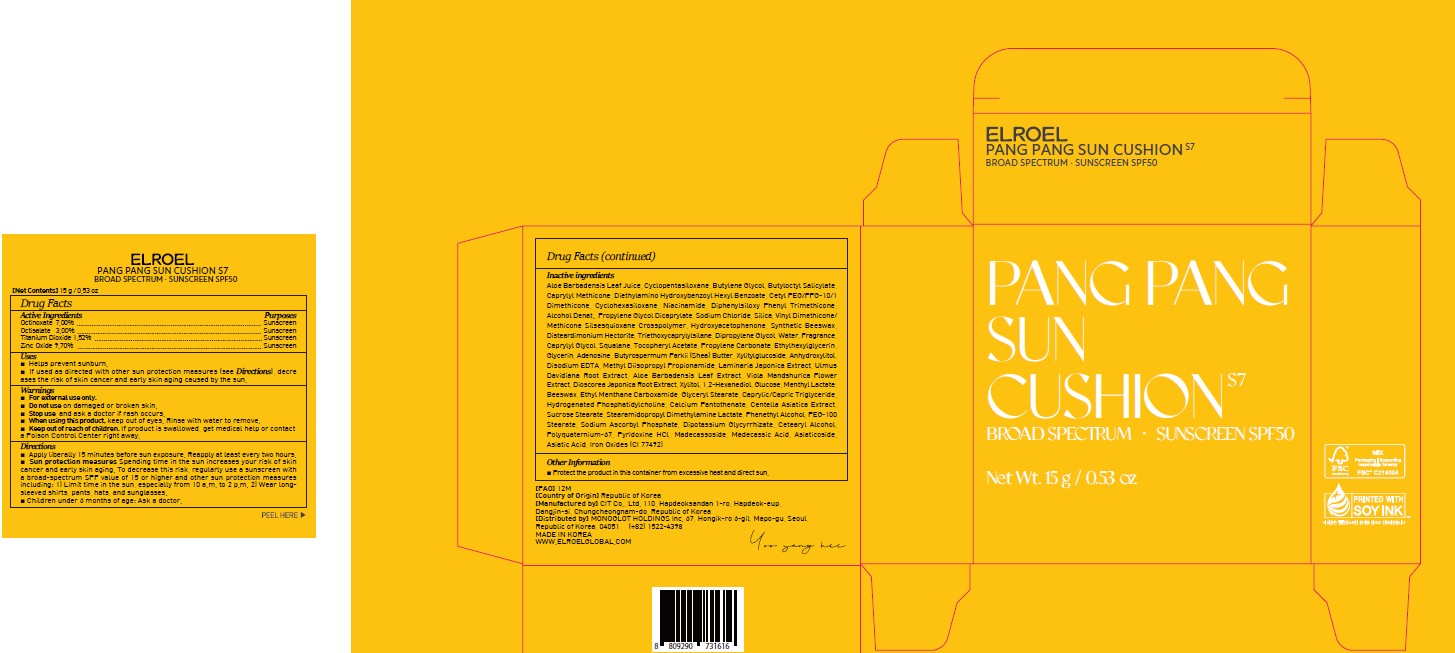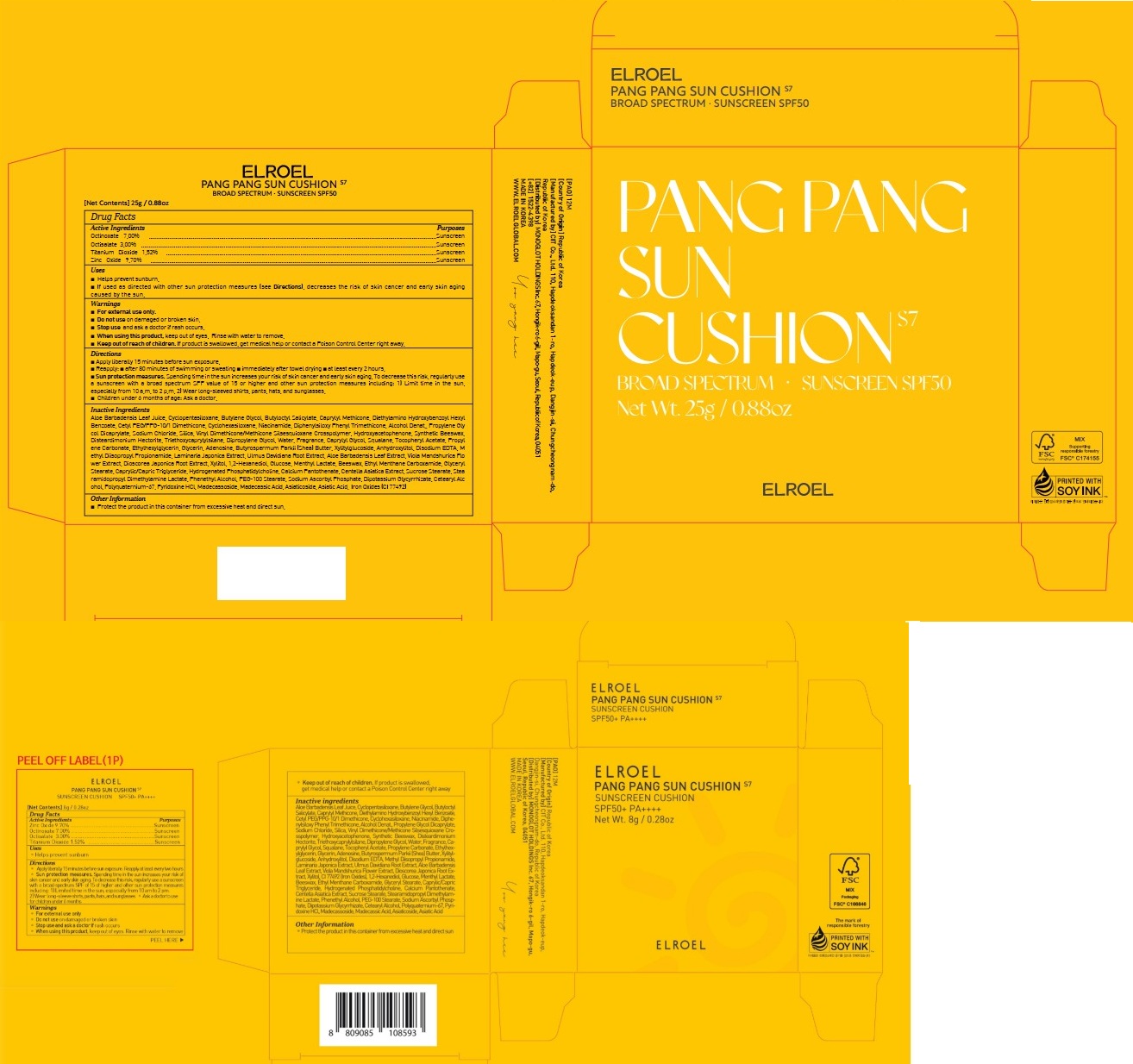 DRUG LABEL: ELROEL Pang Pang Sun Cushion S7
NDC: 83154-003 | Form: CREAM
Manufacturer: MONOGLOT HOLDINGS Inc.
Category: otc | Type: HUMAN OTC DRUG LABEL
Date: 20260205

ACTIVE INGREDIENTS: TITANIUM DIOXIDE 1.52 g/100 g; ZINC OXIDE 9.7 g/100 g; OCTINOXATE 7 g/100 g; OCTISALATE 3 g/100 g
INACTIVE INGREDIENTS: SYNTHETIC BEESWAX; DISTEARDIMONIUM HECTORITE; TRIETHOXYCAPRYLYLSILANE; DIPROPYLENE GLYCOL; WATER; CAPRYLYL GLYCOL; SQUALANE; .ALPHA.-TOCOPHEROL ACETATE; PROPYLENE CARBONATE; ALUMINUM OXIDE; GLYCERIN; ETHYLHEXYLGLYCERIN; SHEA BUTTER; HYDROXYACETOPHENONE; ADENOSINE; XYLITYLGLUCOSIDE; ANHYDROXYLITOL; EDETATE DISODIUM ANHYDROUS; METHYL DIISOPROPYL PROPIONAMIDE; LAMINARIA JAPONICA; ULMUS DAVIDIANA ROOT; VIOLA MANDSHURICA FLOWER; DIOSCOREA JAPONICA TUBER; XYLITOL; FERRIC OXIDE YELLOW; 1,2-HEXANEDIOL; ANHYDROUS DEXTROSE; MENTHYL LACTATE, (-)-; YELLOW WAX; ETHYL MENTHANE CARBOXAMIDE; GLYCERYL MONOSTEARATE; MEDIUM-CHAIN TRIGLYCERIDES; CALCIUM PANTOTHENATE; CENTELLA ASIATICA TRITERPENOIDS; SUCROSE STEARATE; STEARAMIDOPROPYL DIMETHYLAMINE LACTATE; PHENYLETHYL ALCOHOL; PEG-100 STEARATE; SODIUM ASCORBYL PHOSPHATE; CETOSTEARYL ALCOHOL; GLYCYRRHIZINATE DIPOTASSIUM; PYRIDOXINE HYDROCHLORIDE; MADECASSOSIDE; MADECASSIC ACID; ASIATICOSIDE; ASIATIC ACID; ALOE VERA LEAF; CYCLOMETHICONE 5; AMILOXATE; CAPRYLYL TRISILOXANE; BUTYLENE GLYCOL; DIETHYLAMINO HYDROXYBENZOYL HEXYL BENZOATE; CETYL PEG/PPG-10/1 DIMETHICONE (HLB 4); CYCLOMETHICONE 6; NIACINAMIDE; DIPHENYLSILOXY PHENYL TRIMETHICONE; ALCOHOL; PROPYLENE GLYCOL DICAPRYLATE; SODIUM CHLORIDE; SILICON DIOXIDE; VINYL DIMETHICONE/METHICONE SILSESQUIOXANE CROSSPOLYMER

83154-003_ELROEL Pang Pang Sun Cushion S7

ACTIVE INGREDIENT

ZINC OXIDE 9.70%

OCTINOXATE 7.00%
OCTISALATE 3.00%

TITANIUM DIOXIDE 1.52%

PURPOSE

Sunscreen

INDICATIONS AND USAGE

Helps prevent sunburn

DOSAGE AND ADMINISTRATION

For sunscreen use:
■ apply liberally 15 minutes before sun exposure
■ reapply at least every two hours
■ use a water resistant sunscreen if swimming or sweating
■ Sun Protection Measures.
Spending time in the sun increases your risk of skin cancer and early skin aging. To decrease this risk, regularly use a sunscreen with a Broad Spectrum SPF value of 15 or higher and other sun protection measures including:
– limit time in the sun, especially from 10 a.m. – 2 p.m.
– wear long-sleeved shirts, pants, hats and sunglasses
■ children under 6 months of age: ask a doctor

WARNINGS

For external use only.
Do not use on damaged or broken skin.
When using this product, keep out of eyes. Rinse with water to remove.
Stop using and ask a doctor if rash occurs.

KEEP OUT OF REACH OF CHILDREN

Keep out of reach of the children. If product is swallowed, get medical help or contact a poison control center right away.

INACTIVE INGREDIENT

Aloe Barbadensis Leaf JuiceCyclopentasiloxane, Butylene Glycol, Butyloctyl Salicylate, Caprylyl Methicone, Diethylamino Hydroxybenzoyl Hexyl Benzoate, Cetyl PEG/PPG-10/1 Dimethicone, Cyclohexasiloxane, Niacinamide, Diphenylsiloxy Phenyl Trimethicone, Alcohol Denat., Propylene Glycol Dicaprylate, Sodium Chloride, Silica, Vinyl Dimethicone/Methicone Silsesquioxane Crosspolymer, Hydroxyacetophenone, Synthetic Beeswax, Disteardimonium Hectorite, Triethoxycaprylylsilane, Dipropylene Glycol, Water, Fragrance, Caprylyl Glycol, Squalane, Tocopheryl Acetate, Propylene Carbonate, Ethylhexylglycerin, Glycerin, Adenosine, Butyrospermum Parkii (Shea) Butter, Xylitylglucoside, Anhydroxylitol, Disodium EDTA, Methyl Diisopropyl Propionamide, Laminaria Japonica Extract, Ulmus Davidiana Root Extract, Aloe Barbadensis Leaf Extract, Viola Mandshurica Flower Extract, Dioscorea Japonica Root Extract, Xylitol, CI 77492, 1,2-Hexanediol, Glucose, Menthyl Lactate, Beeswax, Ethyl Menthane Carboxamide, Glyceryl Stearate, Caprylic/Capric Triglyceride, Hydrogenated Phosphatidylcholine, Calcium Pantothenate, Centella Asiatica Extract, Sucrose Stearate, Stearamidopropyl Dimethylamine Lactate, Phenethyl Alcohol, PEG-100 Stearate, Sodium Ascorbyl Phosphate, Dipotassium Glycyrrhizate, Cetearyl Alcohol, Polyquaternium-67, Pyridoxine HCl, Madecassoside, Madecassic Acid, Asiaticoside, Asiatic Acid

OTHER SAFETY INFORMATION

Protect the product in this container from excessive heat and direct sunlight